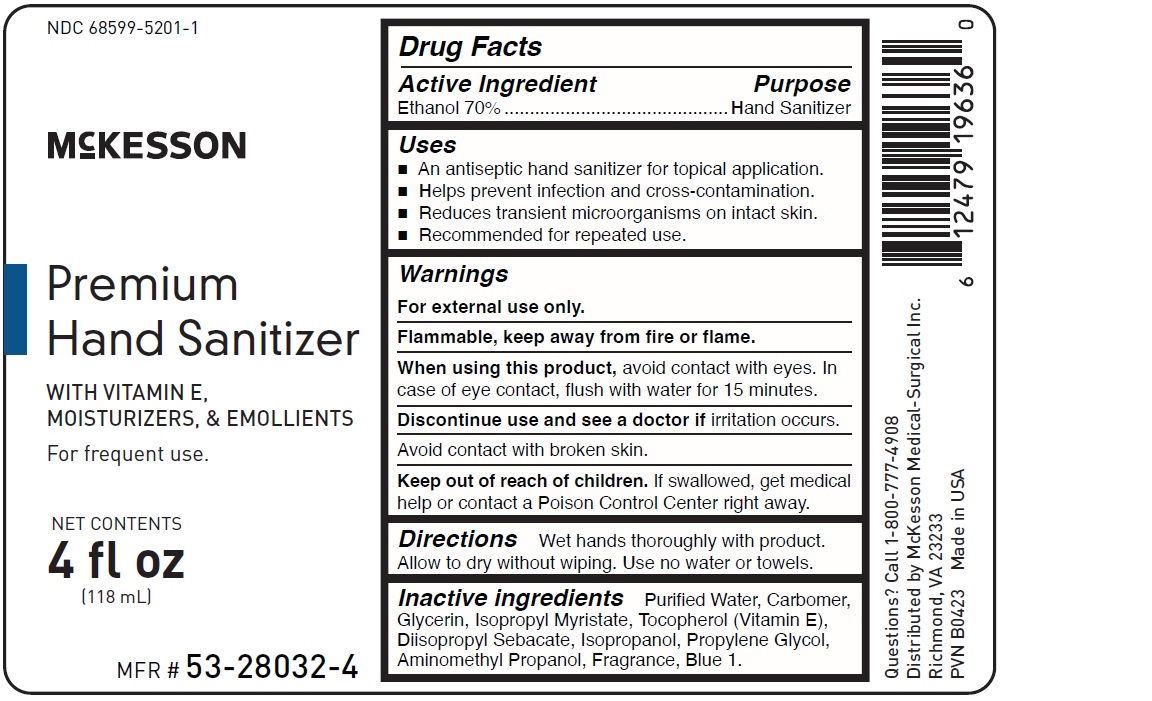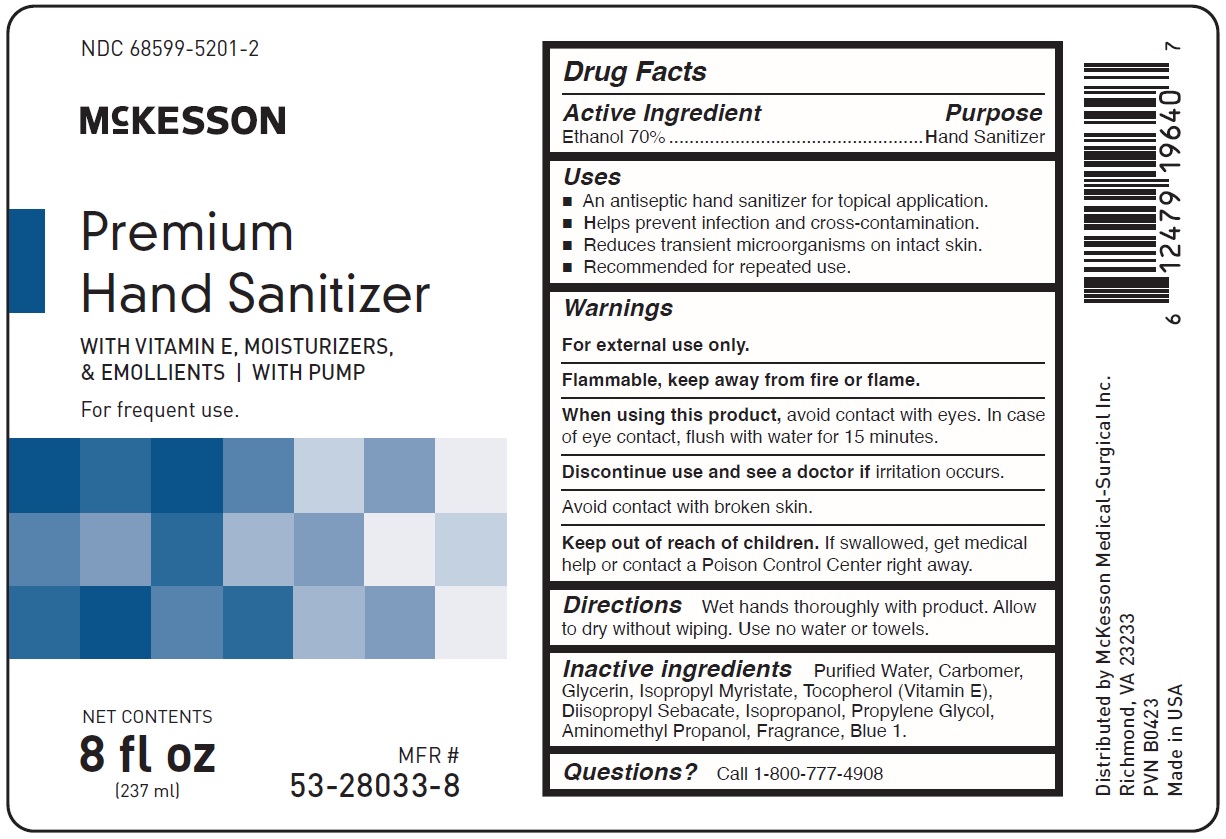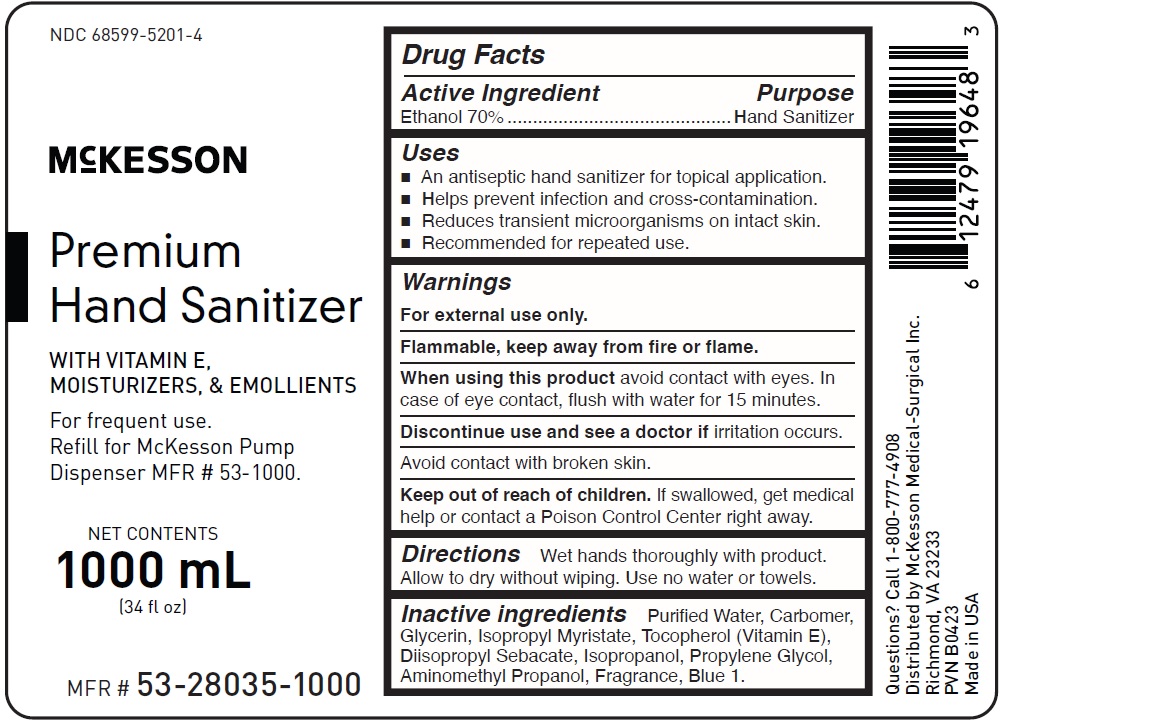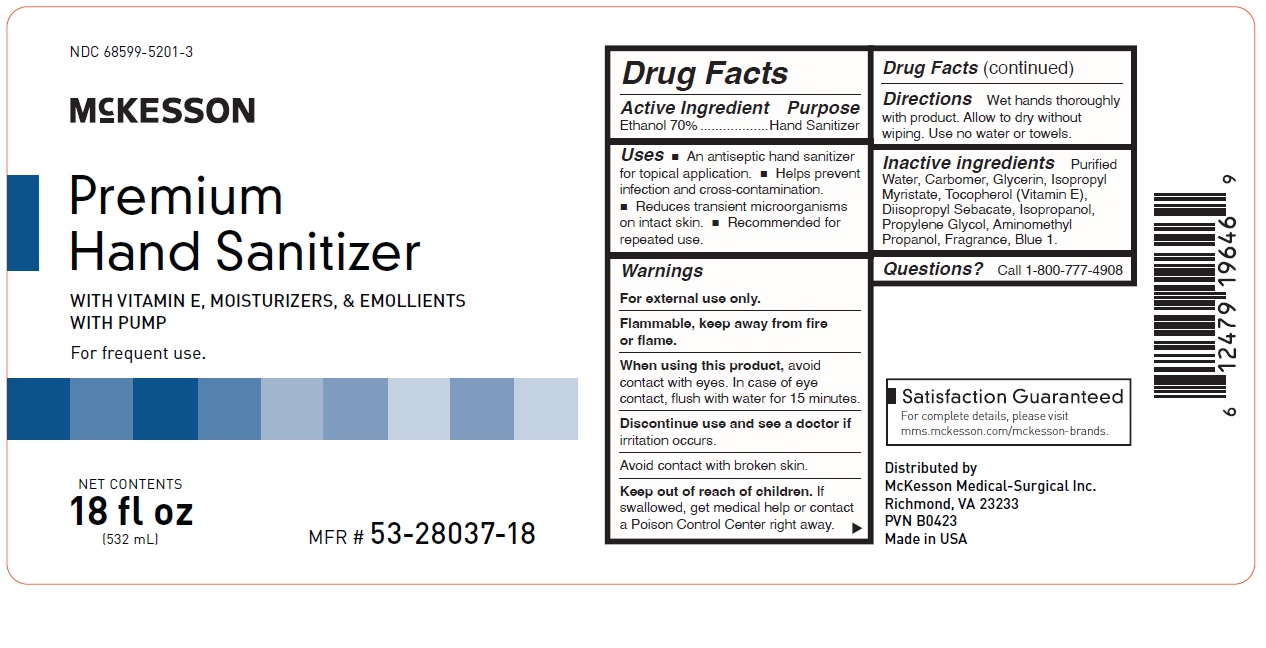 DRUG LABEL: Premium Hand Sanitizer
NDC: 68599-5201 | Form: GEL
Manufacturer: MCKESSON MEDICAL-SURGICAL INC.
Category: otc | Type: HUMAN OTC DRUG LABEL
Date: 20241118

ACTIVE INGREDIENTS: ALCOHOL 70 g/100 g
INACTIVE INGREDIENTS: WATER; CARBOMER COPOLYMER TYPE A; GLYCERIN; ISOPROPYL MYRISTATE; TOCOPHEROL; DIISOPROPYL SEBACATE; ISOPROPYL ALCOHOL; PROPYLENE GLYCOL; AMINOMETHYLPROPANOL; FD&C BLUE NO. 1

Active Ingredient Purpose

Ethanol 70% ...................................... hand sanitizer

Uses

- an antiseptic hand sanitizer for topical application
- helps prevent infection and cross-contamination
- reduces transient microorganisms on intact skin
- recommended for repeated use

Keep out of reach of children. If swallowed, get medical help or contact a Poison Control Center right away.

INDICATIONS AND USAGE

McKesson Premium Hand Sanitizer

With Vitamin E, Moisturizers, & Emollients

For frequent use

Directions

Wet hands thoroughly with product. Allow to dry without wiping. Use no water or towels.

Warnings

For external use only.

Flammable, keep away from fire or flame.

When using this product avoid contact with eyes. In case of eye contact, flush with water for 15 minutes.

Discontinue use and see a doctor if irritation occurs.

Avoid contact with broken skin.

Inactive ingredients

purified water, carbomer, glycerin, isopropyl myristate, tocopherol (vitamin E), diisopropyl sebacate, isopropanol, propylene glycol, aminomethyl propanol, fragrance, blue 1.